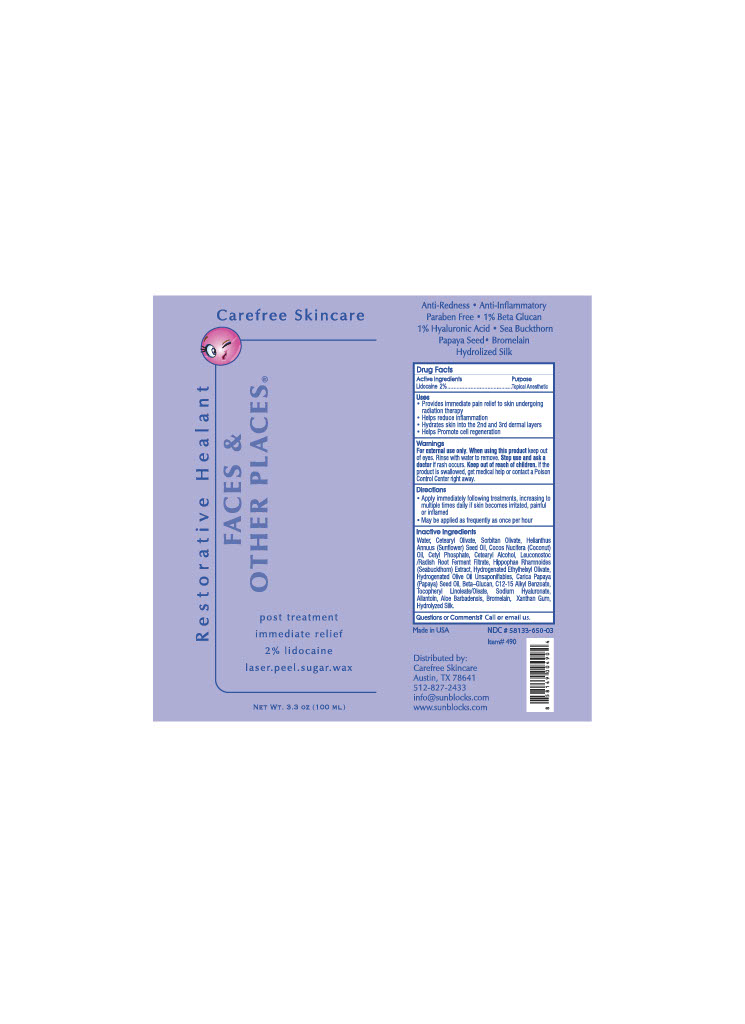 DRUG LABEL: RadX
NDC: 58133-650 | Form: LOTION
Manufacturer: Cosmetic Specialty Labs, Inc.
Category: otc | Type: HUMAN OTC DRUG LABEL
Date: 20210802

ACTIVE INGREDIENTS: LIDOCAINE 2 g/100 mL
INACTIVE INGREDIENTS: .ALPHA.-TOCOPHEROL LINOLEATE, D-; XANTHAN GUM; ALOE VERA LEAF; SILK, ACID HYDROLYZED (1000 MW); ALLANTOIN; ALKYL (C12-15) BENZOATE; PAPAYA; CETOSTEARYL ALCOHOL; SUNFLOWER OIL; ETHYLHEXYL OLEATE; CETEARYL OLIVATE; CETYL PHOSPHATE; COCONUT OIL; HIPPOPHAE RHAMNOIDES FRUIT OIL; HYDROGENATED OLIVE OIL UNSAPONIFIABLES; LEUCONOSTOC/RADISH ROOT FERMENT FILTRATE; SODIUM CARBOXYMETHYL .BETA.-GLUCAN (DS 0.65-0.85); FRUIT BROMELAIN; WATER; HYALURONATE SODIUM; SORBITAN OLIVATE

Active Incredients

Lidocaine 2%

Purpose

Topical Anesthetic

Uses

- Provides immediate pain relief to skin undergoing radiation therapy
- Helps reduce inflammation
- Hydrates skin into the 2nd and 3rd dermal layers
- Helps Promote cell regeneration

Warnings

For external use only.

WHEN USING

keep out of eyes. Rinse with water to remove.

STOP USE

Stop us and ask a doctor if rash occurs.

KEEP OUT OF REACH OF CHILDREN

Keep ouf of reach of children. If the product is swallowed, get medical help or contact a Poison Control Center right away.

Directions

- Apply immediately following treatments, increasing to multiple times daily if skin becomes irritated, painful or inflamed.
- May be applied as frequently as once per hour.

Inactive Ingredients

Water, Cetearyl Olivate, Sorbitan Olivate, Helianthus Annuus (Sunflower) Seed Oil, Cocos Nucifera (Coconut) Oil, Cetyl Phosphate, Cetearyl Alcohol, Leuconostoc/Radish Root Ferment Filtrate, Hippophae Rhamnoides (Sea Buckthorn) Extract, Hydrogenated Ethylhelxyl Olivate, Hydrogenated Olive Oil Unsaponifiables, Carica Papaya (Papaya) Seed Oil, Beta-Glucan, C12-C15 Alkyl Benzoate, Tocopheryl Linoleate/Oleate, Sodium Hyaluronate, Allentoin, Aloe Barbadensis, Bromelain, Xanthan Gum, Hydrolyzed Silk